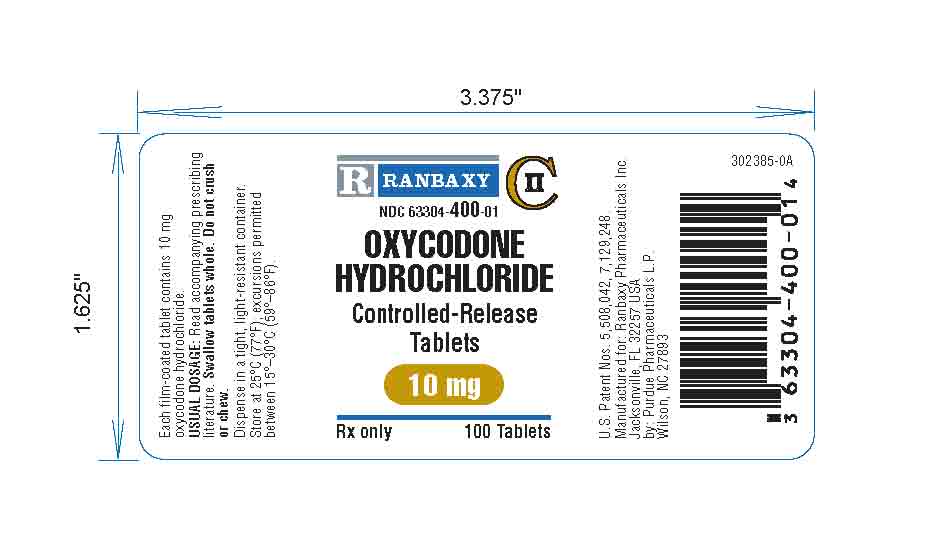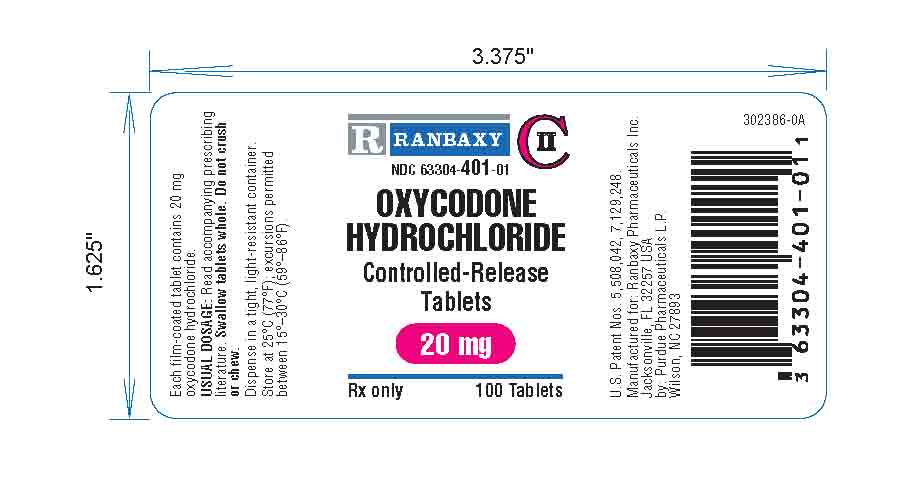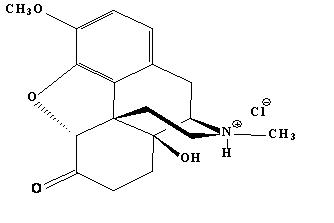 DRUG LABEL: Oxycodone HCl Controlled-Release
NDC: 63304-400 | Form: TABLET
Manufacturer: Ranbaxy Pharmaceuticals Inc
Category: prescription | Type: HUMAN PRESCRIPTION DRUG LABEL
Date: 20100114
DEA Schedule: CII

ACTIVE INGREDIENTS: OXYCODONE HYDROCHLORIDE 10 mg/1 1
INACTIVE INGREDIENTS: HYPROMELLOSE; LACTOSE; MAGNESIUM STEARATE; POLYETHYLENE GLYCOL 400; POVIDONE; SODIUM HYDROXIDE; SORBIC ACID; STEARYL ALCOHOL; TALC; TITANIUM DIOXIDE; TRIACETIN; HYDROXYPROPYL CELLULOSE; EUDRAGIT RS 30

OXYCODONE HCl CONTROLLED-RELEASE TABLETS
10 mg and 20 mg CII
302389-0A

WARNING

Oxycodone HCl Controlled-Release Tablets are an opioid agonist and a Schedule II controlled substance with an abuse liability similar to morphine.

Oxycodone can be abused in a manner similar to other opioid agonists, legal or illicit. This should be considered when prescribing or dispensing Oxycodone HCl Controlled-Release Tablets in situations where the physician or pharmacist is concerned about an increased risk of misuse, abuse, or diversion.

Oxycodone HCl Controlled-Release Tablets are a controlled-release oral formulation of oxycodone hydrochloride indicated for the management of moderate to severe pain when a continuous, around-the-clock analgesic is needed for an extended period of time.

Oxycodone HCl Controlled-Release Tablets are NOT intended for use as a prn analgesic.

OXYCODONE HCl CONTROLLED-RELEASE 80 mg, and 160 mg Tablets, or a single dose greater than 40 mg, ARE FOR USE IN OPIOID-TOLERANT PATIENTS ONLY. A single dose greater than 40 mg, or total daily doses greater than 80 mg, may cause fatal respiratory depression when administered to patients who are not tolerant to the respiratory depressant effects of opioids.

OXYCODONE HCl CONTROLLED-RELEASE TABLETS ARE TO BE SWALLOWED WHOLE AND ARE NOT TO BE BROKEN, CHEWED, OR CRUSHED. TAKING BROKEN, CHEWED, OR CRUSHED OXYCODONE HCl CONTROLLED-RELEASE TABLETS LEADS TO RAPID RELEASE AND ABSORPTION OF A POTENTIALLY FATAL DOSE OF OXYCODONE.

DESCRIPTION

Oxycodone HCl Controlled-Release Tablets are an opioid analgesic supplied in 10 mg and 20 mg tablet strengths for oral administration. The tablet strengths describe the amount of oxycodone per tablet as the hydrochloride salt. The structural formula for oxycodone hydrochloride is as follows:

C18 H21 NO4 • HCl MW 351.83

The chemical formula is 4, 5α-epoxy-14-hydroxy-3-methoxy-17-methylmorphinan-6-one hydrochloride.

Oxycodone is a white, odorless crystalline powder derived from the opium alkaloid, thebaine. Oxycodone hydrochloride dissolves in water (1 g in 6 to 7 mL). It is slightly soluble in alcohol (octanol water partition coefficient 0.7). The tablets contain the following inactive ingredients: ammonio methacrylate copolymer, hypromellose, lactose, magnesium stearate, polyethylene glycol 400, povidone, sodium hydroxide, sorbic acid, stearyl alcohol, talc, titanium dioxide, and triacetin.

The 10 mg tablets also contain: hydroxypropyl cellulose.

The 20 mg tablets also contain: polysorbate 80 and red iron oxide.

Oxycodone HCL controlled-release 10 mg and 20 mg tablets are tested using USP dissolution test 2 and meet the associated tolerances provided in acceptance table 2 of the oxycodone hydrochloride extended-release tablets USP monograph.

CLINICAL PHARMACOLOGY

Oxycodone is a pure agonist opioid whose principal therapeutic action is analgesia. Other members of the class known as opioid agonists include substances such as morphine, hydromorphone, fentanyl, codeine, and hydrocodone. Pharmacological effects of opioid agonists include anxiolysis, euphoria, feelings of relaxation, respiratory depression, constipation, miosis, and cough suppression, as well as analgesia. Like all pure opioid agonist analgesics, with increasing doses there is increasing analgesia, unlike with mixed agonist/antagonists or non-opioid analgesics, where there is a limit to the analgesic effect with increasing doses. With pure opioid agonist analgesics, there is no defined maximum dose; the ceiling to analgesic effectiveness is imposed only by side effects, the more serious of which may include somnolence and respiratory depression.

Central Nervous System

The precise mechanism of the analgesic action is unknown. However, specific CNS opioid receptors for endogenous compounds with opioid-like activity have been identified throughout the brain and spinal cord and play a role in the analgesic effects of this drug.

Oxycodone produces respiratory depression by direct action on brain stem respiratory centers. The respiratory depression involves both a reduction in the responsiveness of the brain stem respiratory centers to increases in carbon dioxide tension and to electrical stimulation.

Oxycodone depresses the cough reflex by direct effect on the cough center in the medulla. Antitussive effects may occur with doses lower than those usually required for analgesia.

Oxycodone causes miosis, even in total darkness. Pinpoint pupils are a sign of opioid overdose but are not pathognomonic (e.g., pontine lesions of hemorrhagic or ischemic origin may produce similar findings). Marked mydriasis rather than miosis may be seen with hypoxia in the setting of Oxycodone HCl Controlled-Release Tablets overdose (See OVERDOSAGE).

Gastrointestinal Tract And Other Smooth Muscle

Oxycodone causes a reduction in motility associated with an increase in smooth muscle tone in the antrum of the stomach and duodenum. Digestion of food in the small intestine is delayed and propulsive contractions are decreased. Propulsive peristaltic waves in the colon are decreased, while tone may be increased to the point of spasm resulting in constipation. Other opioid-induced effects may include a reduction in gastric, biliary and pancreatic secretions, spasm of sphincter of Oddi, and transient elevations in serum amylase.

Cardiovascular System

Oxycodone may produce release of histamine with or without associated peripheral vasodilation. Manifestations of histamine release and/or peripheral vasodilation may include pruritus, flushing, red eyes, sweating, and/or orthostatic hypotension.

Concentration – Efficacy Relationships

Studies in normal volunteers and patients reveal predictable relationships between oxycodone dosage and plasma oxycodone concentrations, as well as between concentration and certain expected opioid effects, such as pupillary constriction, sedation, overall “drug effect”, analgesia and feelings of “relaxation”.

As with all opioids, the minimum effective plasma concentration for analgesia will vary widely among patients, especially among patients who have been previously treated with potent agonist opioids. As a result, patients must be treated with individualized titration of dosage to the desired effect. The minimum effective analgesic concentration of oxycodone for any individual patient may increase over time due to an increase in pain, the development of a new pain syndrome and/or the development of analgesic tolerance.

Concentration – Adverse Experience Relationships

Oxycodone HCl Controlled-Release Tablets are associated with typical opioid-related adverse experiences. There is a general relationship between increasing oxycodone plasma concentration and increasing frequency of dose-related opioid adverse experiences such as nausea, vomiting, CNS effects, and respiratory depression. In opioid-tolerant patients, the situation is altered by the development of tolerance to opioid-related side effects, and the relationship is not clinically relevant.

As with all opioids, the dose must be individualized (see DOSAGE AND ADMINISTRATION), because the effective analgesic dose for some patients will be too high to be tolerated by other patients.

PHARMACOKINETICS AND METABOLISM

The activity of Oxycodone HCl Controlled-Release Tablets is primarily due to the parent drug oxycodone. Oxycodone HCl Controlled-Release Tablets are designed to provide controlled delivery of oxycodone over 12 hours.

Breaking, chewing or crushing Oxycodone HCl Controlled-Release Tablets eliminates the controlled delivery mechanism and results in the rapid release and absorption of a potentially fatal dose of oxycodone.

Oxycodone release from Oxycodone HCl Controlled-Release Tablets is pH independent. Oxycodone is well absorbed from Oxycodone HCl Controlled-Release Tablets with an oral bioavailability of 60% to 87%. The relative oral bioavailability of Oxycodone HCl Controlled-Release Tablets to immediate-release oral dosage forms is 100%. Upon repeated dosing in normal volunteers in pharmacokinetic studies, steady-state levels were achieved within 24-36 hours. Dose proportionality and/or bioavailability has been established for the 10 mg, 20 mg, 40 mg, 80 mg, and 160 mg tablet strengths for both peak plasma levels (Cmax) and extent of absorption (AUC). Oxycodone is extensively metabolized and eliminated primarily in the urine as both conjugated and unconjugated metabolites. The apparent elimination half-life of oxycodone following the administration of Oxycodone HCl Controlled-Release Tablets was 4.5 hours compared to 3.2 hours for immediate-release oxycodone.

Absorption

About 60% to 87% of an oral dose of oxycodone reaches the central compartment in comparison to a parenteral dose. This high oral bioavailability is due to low pre-systemic and/or first-pass metabolism. In normal volunteers, the t½ of absorption is 0.4 hours for immediate-release oral oxycodone. In contrast, Oxycodone HCl Controlled-Release Tablets exhibit a biphasic absorption pattern with two apparent absorption half-lives of 0.6 and 6.9 hours, which describes the initial release of oxycodone from the tablet followed by a prolonged release.

Plasma Oxycodone by Time

Dose proportionality has been established for the 10 mg, 20 mg, 40 mg, and 80 mg tablet strengths for both peak plasma concentrations (Cmax) and extent of absorption (AUC) (see Table 1 below). Another study established that the 160 mg tablet is bioequivalent to 2 x 80 mg tablets as well as to 4 x 40 mg for both peak plasma concentrations (Cmax) and extent of absorption (AUC) (see Table 2 below). Given the short half-life of elimination of oxycodone from Oxycodone HCl Controlled-Release Tablets, steady-state plasma concentrations of oxycodone are achieved within 24-36 hours of initiation of dosing with Oxycodone HCl Controlled-Release Tablets. In a study comparing 10 mg of Oxycodone HCl Controlled-Release Tablets every 12 hours to 5 mg of immediate-release oxycodone every 6 hours, the two treatments were found to be equivalent for AUC and Cmax, and similar for Cmin (trough) concentrations.

TABLE 1 Mean [% coefficient variation]
Regimen/Dosage Form | AUC (ng•hr/mL)† | x (ng/mL) | x (hrs) | Trough Conc. (ng/mL)
Single Dose 10 mg Oxycodone HCl Controlled-Release Tablets | 100.7 [26.6] | 10.6 [20.1] | 2.7 [44.1] | n.a.
20 mg Oxycodone HCl Controlled-Release Tablets | 207.5 [35.9] | 21.4 [36.6] | 3.2 [57.9] | n.a.
40 mg Oxycodone HCl Controlled-Release Tablets | 423.1 [33.3] | 39.3 [34.0] | 3.1 [77.4] | n.a.
80 mg Oxycodone HCl Controlled-Release Tablets | 1085.5 [32.3] | 98.5 [32.1] | 2.1 [52.3] | n.a.
Multiple Dose 10 mg Oxycodone HCl Controlled-Release Tablets q12h | 103.6[38.6] | 15.1 [31.0] | 3.2 [69.5] | 7.2 [48.1]
5 mg immediate-release q6h | 90.0 [36.2] | 15.5 [28.8] | 1.6 [49.7] | 7.4 [50.9]

TABLE 2 Mean [% coefficient variation]
Regimen/ | Dosage Form | AUC∞ (ng•hr/mL)† | Cmax (ng/mL) | Tmax (hrs) | Trough Conc. (ng/mL)
Single Dose | 4 x 40 mg Oxycodone HCl Controlled- Release Tablets* | 1935.3 [34.7] | 152.0 [28.9] | 2.56 [42.3] | n.a.
 | 2 x 80 mg Oxycodone HCl Controlled- Release Tablets* | 1859.3 [30.1] | 153.4 [25.1] | 2.78 [69.3] | n.a.
 | 1 x 160 mg Oxycodone HCl Controlled-Release Tablets* | 1856.4 [30.5] | 156.4 [24.8] | 2.54 [36.4] | n.a.
† for single-dose AUC = AUC0-inf; for multiple-dose AUC = AUC0-T
* data obtained while volunteers received naltrexone which can enhance absorption

Oxycodone HCl Controlled-Release Tablets are NOT INDICATED FOR RECTAL ADMINISTRATION. Data from a study involving 21 normal volunteers show that Oxycodone HCl Controlled-Release Tablets administered per rectum resulted in an AUC 39% greater and a Cmax 9% higher than tablets administered by mouth. Therefore, there is an increased risk of adverse events with rectal administration.

Food Effects

Food has no significant effect on the extent of absorption of oxycodone from Oxycodone HCl Controlled-Release Tablets. However, the peak plasma concentration of oxycodone increased by 25% when an Oxycodone HCl Controlled-Release Tablets 160 mg Tablet was administered with a high-fat meal.

Distribution

Following intravenous administration, the volume of distribution (Vss) for oxycodone was 2.6 L/kg. Oxycodone binding to plasma protein at 37°C and a pH of 7.4 was about 45%. Once absorbed, oxycodone is distributed to skeletal muscle, liver, intestinal tract, lungs, spleen, and brain. Oxycodone has been found in breast milk (see PRECAUTIONS).

Metabolism

Oxycodone hydrochloride is extensively metabolized to noroxycodone, oxymorphone, noroxymorphone, and their glucuronides. The major circulating metabolite is noroxycodone. Noroxycodone is reported to be a considerably weaker analgesic than oxycodone. Oxymorphone, although possessing analgesic activity, is present in the plasma only in low concentrations. The correlation between oxymorphone concentrations and opioid effects was much less than that seen with oxycodone plasma concentrations. The analgesic activity profile of other metabolites is not known.

CYP3A mediated N-demethylation (to noroxycodone) is the primary metabolic pathway of oxycodone with a lower contribution from CYP2D6 mediated O-demethylation (to oxymorphone). Therefore, the formation of these and related metabolites can, in theory, be affected by other drugs (see Drug-Drug Interactions).

Excretion

Oxycodone and its metabolites are excreted primarily via the kidney. The amounts measured in the urine have been reported as follows: free oxycodone up to 19%; conjugated oxycodone up to 50%; free oxymorphone 0%; conjugated oxymorphone ≤ 14%; both free and conjugated noroxycodone have been found in the urine but not quantified. The total plasma clearance was 0.8 L/min for adults.

Special Populations

Elderly

The plasma concentrations of oxycodone are only nominally affected by age, being 15% greater in elderly as compared to young subjects.

Gender

Female subjects have, on average, plasma oxycodone concentrations up to 25% higher than males on a body weight adjusted basis. The reason for this difference is unknown.

Renal Impairment

Data from a pharmacokinetic study involving 13 patients with mild to severe renal dysfunction (creatinine clearance <60 mL/min) show peak plasma oxycodone and noroxycodone concentrations 50% and 20% higher, respectively, and AUC values for oxycodone, noroxycodone, and oxymorphone 60%, 50%, and 40% higher than normal subjects, respectively. This is accompanied by an increase in sedation but not by differences in respiratory rate, pupillary constriction, or several other measures of drug effect. There was an increase in t½ of elimination for oxycodone of only 1 hour (see PRECAUTIONS).

Hepatic Impairment

Data from a study involving 24 patients with mild to moderate hepatic dysfunction show peak plasma oxycodone and noroxycodone concentrations 50% and 20% higher, respectively, than normal subjects. AUC values are 95% and 65% higher, respectively. Oxymorphone peak plasma concentrations and AUC values are lower by 30% and 40%. These differences are accompanied by increases in some, but not other, drug effects. The t½ elimination for oxycodone increased by 2.3 hours (see PRECAUTIONS).

Drug-Drug Interactions (see PRECAUTIONS)

CYP3A mediated N-demethylation is the principal metabolic pathway of oxycodone with a lower contribution from CYP2D6 mediated O-demethylation and in theory can be affected by drugs affecting cytochrome P450 enzymes.

Oxycodone is metabolized in part by cytochrome P450 2D6 to oxymorphone which represents less than 15% of the total administered dose. This route of elimination may be blocked by a variety of drugs (e.g., certain cardiovascular drugs including amiodarone and quinidine as well as polycyclic anti-depressants). However, in a study involving 10 subjects using quinidine, a known inhibitor of cytochrome P450 2D6, the pharmacodynamic effects of oxycodone were unchanged.

Pharmacodynamics

A single-dose, double-blind, placebo- and dose-controlled study was conducted using Oxycodone HCl Controlled-Release Tablets (10, 20, and 30 mg) in an analgesic pain model involving 182 patients with moderate to severe pain. Twenty and 30 mg of Oxycodone HCl Controlled-Release Tablets were superior in reducing pain compared with placebo, and this difference was statistically significant. The onset of analgesic action with Oxycodone HCl Controlled-Release Tablets occurred within 1 hour in most patients following oral administration.

CLINICAL TRIALS

A double-blind placebo-controlled, fixed-dose, parallel group, two-week study was conducted in 133 patients with chronic, moderate to severe pain, who were judged as having inadequate pain control with their current therapy. In this study, 20 mg Oxycodone HCl Controlled-Release Tablets q12h but not 10 mg Oxycodone HCl Controlled-Release Tablets q12h decreased pain compared with placebo, and this difference was statistically significant.

INDICATIONS AND USAGE

Oxycodone HCl Controlled-Release Tablets are a controlled-release oral formulation of oxycodone hydrochloride indicated for the management of moderate to severe pain when a continuous, around-the-clock analgesic is needed for an extended period of time.

Oxycodone HCl Controlled-Release Tablets are NOT intended for use as a prn analgesic.

Physicians should individualize treatment in every case, initiating therapy at the appropriate point along a progression from non-opioid analgesics, such as non-steroidal anti-inflammatory drugs and acetaminophen to opioids in a plan of pain management such as outlined by the World Health Organization, the Agency for Healthcare Research and Quality (formerly known as the Agency for Health Care Policy and Research), the Federation of State Medical Boards Model Guidelines, or the American Pain Society.

Oxycodone HCl Controlled-Release Tablets are not indicated for pain in the immediate postoperative period (the first 12-24 hours following surgery), or if the pain is mild, or not expected to persist for an extended period of time. Oxycodone HCl Controlled-Release Tablets are only indicated for postoperative use if the patient is already receiving the drug prior to surgery or if the postoperative pain is expected to be moderate to severe and persist for an extended period of time. Physicians should individualize treatment, moving from parenteral to oral analgesics as appropriate. (See American Pain Society guidelines.)

CONTRAINDICATIONS

Oxycodone HCl Controlled-Release Tablets are contraindicated in patients with known hypersensitivity to oxycodone, or in any situation where opioids are contraindicated. This includes patients with significant respiratory depression (in unmonitored settings or the absence of resuscitative equipment), and patients with acute or severe bronchial asthma or hypercarbia. Oxycodone HCl Controlled-Release Tablets are contraindicated in any patient who has or is suspected of having paralytic ileus.

WARNINGS

OXYCODONE HCl CONTROLLED-RELEASE TABLETS ARE TO BE SWALLOWED WHOLE AND ARE NOT TO BE BROKEN, CHEWED, OR CRUSHED. TAKING BROKEN, CHEWED, OR CRUSHED OXYCODONE HCl CONTROLLED-RELEASE TABLETS LEADS TO RAPID RELEASE AND ABSORPTION OF A POTENTIALLY FATAL DOSE OF OXYCODONE.

Oxycodone HCl Controlled-Release 80 mg Tablets, or a single dose greater than 40 mg, ARE FOR USE IN OPIOID-TOLERANT PATIENTS ONLY. A single dose greater than 40 mg, or total daily doses greater than 80 mg, may cause fatal respiratory depression when administered to patients who are not tolerant to the respiratory depressant effects of opioids.

PATIENTS SHOULD BE INSTRUCTED AGAINST USE BY INDIVIDUALS OTHER THAN THE PATIENT FOR WHOM IT WAS PRESCRIBED, AS SUCH INAPPROPRIATE USE MAY HAVE SEVERE MEDICAL CONSEQUENCES, INCLUDING DEATH.

Misuse, Abuse and Diversion of Opioids

Oxycodone is an opioid agonist of the morphine-type. Such drugs are sought by drug abusers and people with addiction disorders and are subject to criminal diversion.

Oxycodone can be abused in a manner similar to other opioid agonists, legal or illicit. This should be considered when prescribing or dispensing Oxycodone HCl Controlled-Release Tablets in situations where the physician or pharmacist is concerned about an increased risk of misuse, abuse, or diversion.

Oxycodone HCl Controlled-Release Tablets have been reported as being abused by crushing, chewing, snorting, or injecting the dissolved product. These practices will result in the uncontrolled delivery of the opioid and pose a significant risk to the abuser that could result in overdose and death (see WARNINGS and DRUG ABUSE AND ADDICTION).

Concerns about abuse, addiction, and diversion should not prevent the proper management of pain.

Healthcare professionals should contact their State Professional Licensing Board, or State Controlled Substances Authority for information on how to prevent and detect abuse or diversion of this product.

Interactions with Alcohol and Drugs of Abuse

Oxycodone may be expected to have additive effects when used in conjunction with alcohol, other opioids, or illicit drugs that cause central nervous system depression.

DRUG ABUSE AND ADDICTION

Oxycodone HCl Controlled-Release Tablets contain Oxycodone which is a full mu-agonist opiod with an abuse liability similar to morphine and is a schedule II controlled substance. Oxycodone, like morphine and other opiods used in analgesia, can be abused and is subject to criminal diversion.

Drug addiction is characterized by compulsive use, use for non-medical purposes, and continued use despite harm or risk of harm. There is a potential for drug addiction to develop following exposure to opioids, including oxycodone. Drug addiction is a treatable disease, utilizing a multi-disciplinary approach, but relapse is common.

“Drug-seeking” behavior is very common in addicts and drug abusers. Drug-seeking tactics include emergency calls or visits near the end of office hours, refusal to undergo appropriate examination, testing or referral, repeated “loss” of prescriptions, tampering with prescriptions and reluctance to provide prior medical records or contact information for other treating physician(s). “Doctor shopping” to obtain additional prescriptions is common among drug abusers and people suffering from untreated addiction.

Abuse and addiction are separate and distinct from physical dependence and tolerance. Physicians should be aware that addiction may not be accompanied by concurrent tolerance and symptoms of physical dependence in all addicts. In addition, abuse of opioids can occur in the absence of true addiction and is characterized by misuse for non-medical purposes, often in combination with other psychoactive substances. Oxycodone HCl Controlled-Release Tablets, like other opioids, have been diverted for non-medical use. Careful record-keeping of prescribing information, including quantity, frequency, and renewal requests is strongly advised.

Proper assessment of the patient, proper prescribing practices, periodic re-evaluation of therapy, and proper dispensing and storage are appropriate measures that help to limit abuse of opioid drugs.

Oxycodone HCl Controlled-Release Tablets consist of a dual-polymer matrix, intended for oral use only. Abuse of the crushed tablet poses a hazard of overdose and death. This risk is increased with concurrent abuse of alcohol and other substances. With parenteral abuse, the tablet excipients, especially talc, can be expected to result in local tissue necrosis, infection, pulmonary granulomas, and increased risk of endocarditis and valvular heart injury. Parenteral drug abuse is commonly associated with transmission of infectious diseases such as hepatitis and HIV.

Respiratory Depression

Respiratory depression is the chief hazard from oxycodone, the active ingredient in Oxycodone HCl Controlled-Release Tablets, as with all opioid agonists. Respiratory depression is a particular problem in elderly or debilitated patients, usually following large initial doses in non-tolerant patients, or when opioids are given in conjunction with other agents that depress respiration.

Oxycodone should be used with extreme caution in patients with significant chronic obstructive pulmonary disease or cor pulmonale, and in patients having a substantially decreased respiratory reserve, hypoxia, hypercapnia, or pre-existing respiratory depression. In such patients, even usual therapeutic doses of oxycodone may decrease respiratory drive to the point of apnea. In these patients alternative non-opioid analgesics should be considered, and opioids should be employed only under careful medical supervision at the lowest effective dose.

Head Injury

The respiratory depressant effects of opioids include carbon dioxide retention and secondary elevation of cerebrospinal fluid pressure, and may be markedly exaggerated in the presence of head injury, intracranial lesions, or other sources of pre-existing increased intracranial pressure. Oxycodone produces effects on pupillary response and consciousness which may obscure neurologic signs of further increases in intracranial pressure in patients with head injuries.

Hypotensive Effect

Oxycodone HCl Controlled-Release Tablets may cause severe hypotension. There is an added risk to individuals whose ability to maintain blood pressure has been compromised by a depleted blood volume, or after concurrent administration with drugs such as phenothiazines or other agents which compromise vasomotor tone. Oxycodone may produce orthostatic hypotension in ambulatory patients. Oxycodone, like all opioid analgesics of the morphine-type, should be administered with caution to patients in circulatory shock, since vasodilation produced by the drug may further reduce cardiac output and blood pressure.

PRECAUTIONS

General

Opioid analgesics have a narrow therapeutic index in certain patient populations, especially when combined with CNS depressant drugs, and should be reserved for cases where the benefits of opioid analgesia outweigh the known risks of respiratory depression, altered mental state, and postural hypotension.

Use of Oxycodone HCl Controlled-Release Tablets is associated with increased potential risks and should be used only with caution in the following conditions: acute alcoholism; adrenocortical insufficiency (e.g., Addison's disease); CNS depression or coma; delirium tremens; debilitated patients; kyphoscoliosis associated with respiratory depression; myxedema or hypothyroidism; prostatic hypertrophy or urethral stricture; severe impairment of hepatic, pulmonary or renal function; and toxic psychosis.

The administration of oxycodone may obscure the diagnosis or clinical course in patients with acute abdominal conditions. Oxycodone may aggravate convulsions in patients with convulsive disorders, and all opioids may induce or aggravate seizures in some clinical settings.

Interactions with other CNS Depressants

Oxycodone HCl Controlled-Release Tablets should be used with caution and started in a reduced dosage (1/3 to 1/2 of the usual dosage) in patients who are concurrently receiving other central nervous system depressants including sedatives or hypnotics, general anesthetics, phenothiazines, other tranquilizers, and alcohol. Interactive effects resulting in respiratory depression, hypotension, profound sedation, or coma may result if these drugs are taken in combination with the usual doses of Oxycodone HCl Controlled-Release Tablets.

Interactions with Mixed Agonist/Antagonist Opioid Analgesics

Agonist/antagonist analgesics (i.e., pentazocine, nalbuphine, and butorphanol) should be administered with caution to a patient who has received or is receiving a course of therapy with a pure opioid agonist analgesic such as oxycodone. In this situation, mixed agonist/antagonist analgesics may reduce the analgesic effect of oxycodone and/or may precipitate withdrawal symptoms in these patients.

Ambulatory Surgery and Postoperative Use

Oxycodone HCl Controlled-Release Tablets are not indicated for pre-emptive analgesia (administration pre-operatively for the management of postoperative pain).

Oxycodone HCl Controlled-Release Tablets are not indicated for pain in the immediate postoperative period (the first 12 to 24 hours following surgery) for patients not previously taking the drug, because its safety in this setting has not been established.

Oxycodone HCl Controlled-Release Tablets are not indicated for pain in the postoperative period if the pain is mild or not expected to persist for an extended period of time.

Oxycodone HCl Controlled-Release Tablets are only indicated for postoperative use if the patient is already receiving the drug prior to surgery or if the postoperative pain is expected to be moderate to severe and persist for an extended period of time. Physicians should individualize treatment, moving from parenteral to oral analgesics as appropriate (See American Pain Society guidelines).

Patients who are already receiving Oxycodone HCl Controlled-Release Tablets as part of ongoing analgesic therapy may be safely continued on the drug if appropriate dosage adjustments are made considering the procedure, other drugs given, and the temporary changes in physiology caused by the surgical intervention (see DOSAGE AND ADMINISTRATION).

Oxycodone HCl Controlled-Release Tablets and other morphine-like opioids have been shown to decrease bowel motility. Ileus is a common postoperative complication, especially after intra-abdominal surgery with opioid analgesia. Caution should be taken to monitor for decreased bowel motility in postoperative patients receiving opioids. Standard supportive therapy should be implemented.

Use in Pancreatic/Biliary Tract Disease

Oxycodone may cause spasm of the sphincter of Oddi and should be used with caution in patients with biliary tract disease, including acute pancreatitis. Opioids like oxycodone may cause increases in the serum amylase level.

Tolerance and Physical Dependence

Tolerance is the need for increasing doses of opioids to maintain a defined effect such as analgesia (in the absence of disease progression or other external factors). Physical dependence is manifested by withdrawal symptoms after abrupt discontinuation of a drug or upon administration of an antagonist. Physical dependence and tolerance are not unusual during chronic opioid therapy.

The opioid abstinence or withdrawal syndrome is characterized by some or all of the following: restlessness, lacrimation, rhinorrhea, yawning, perspiration, chills, myalgia, and mydriasis. Other symptoms also may develop, including: irritability, anxiety, backache, joint pain, weakness, abdominal cramps, insomnia, nausea, anorexia, vomiting, diarrhea, or increased blood pressure, respiratory rate, or heart rate.

In general, opioids should not be abruptly discontinued (see DOSAGEAND ADMINISTRATION: Cessation of Therapy).

Information for Patients/Caregivers

If clinically advisable, patients receiving Oxycodone HCl Controlled-Release Tablets or their caregivers should be given the following information by the physician, nurse, pharmacist, or caregiver:

1. Patients should be aware that Oxycodone HCl Controlled-Release Tablets contain oxycodone, which is a morphine-like substance.
2. Patients should be advised that Oxycodone HCl Controlled-Release Tablets were designed to work properly only if swallowed whole. Oxycodone HCl Controlled-Release Tablets will release all their contents at once if broken, chewed, or crushed, resulting in a risk of fatal overdose.
3. Patients should be advised to report episodes of breakthrough pain and adverse experiences occurring during therapy. Individualization of dosage is essential to make optimal use of this medication.
4. Patients should be advised not to adjust the dose of Oxycodone HCl Controlled-Release Tablets without consulting the prescribing professional.
5. Patients should be advised that Oxycodone HCl Controlled-Release Tablets may impair mental and/or physical ability required for the performance of potentially hazardous tasks (e.g., driving, operating heavy machinery).
6. Patients should not combine Oxycodone HCl Controlled-Release Tablets with alcohol or other central nervous system depressants (sleep aids, tranquilizers) except by the orders of the prescribing physician, because dangerous additive effects may occur, resulting in serious injury or death.
7. Women of childbearing potential who become, or are planning to become, pregnant should be advised to consult their physician regarding the effects of analgesics and other drug use during pregnancy on themselves and their unborn child.
8. Patients should be advised that Oxycodone HCl Controlled-Release Tablets are a potential drug of abuse. They should protect it from theft, and it should never be given to anyone other than the individual for whom it was prescribed.
9. Patients should be advised that they may pass empty matrix "ghosts" (tablets) via colostomy or in the stool, and that this is of no concern since the active medication has already been absorbed.
10. Patients should be advised that if they have been receiving treatment with Oxycodone HCl Controlled-Release Tablets for more than a few weeks and cessation of therapy is indicated, it may be appropriate to taper the Oxycodone HCl Controlled-Release Tablets dose, rather than abruptly discontinue it, due to the risk of precipitating withdrawal symptoms. Their physician can provide a dose schedule to accomplish a gradual discontinuation of the medication.
11. Patients should be instructed to keep Oxycodone HCl Controlled-Release Tablets in a secure place out of the reach of children. When Oxycodone HCl Controlled-Release Tablets are no longer needed, the unused tablets should be destroyed by flushing down the toilet.

Use in Drug and Alcohol Addiction

Oxycodone HCl Controlled-Release Tablets are an opioid with no approved use in the management of addictive disorders. Its proper usage in individuals with drug or alcohol dependence, either active or in remission, is for the management of pain requiring opioid analgesia.

Drug-Drug Interactions

Opioid analgesics, including Oxycodone HCl Controlled-Release Tablets, may enhance the neuromuscular blocking action of skeletal muscle relaxants and produce an increased degree of respiratory depression.

Inhibitors of CYP3A4:

Since the CYP3A4 isoenzyme plays a major role in the metabolism of oxycodone, co-administration of drugs that inhibit CYP3A4 activity, such as macrolide antibiotics (e.g., erythromycin), azole-antifungal agents (e.g., ketoconazole), and protease inhibitors (e.g., ritonavir), may cause decreased clearance of oxycodone which could lead to an increase in oxycodone plasma concentrations. Although clinical studies have not been conducted, the expected clinical results would be increased or prolonged opioid effects. If co-administration with Oxycodone HCl Controlled-Release Tablets is necessary, caution is advised when initiating therapy with, currently taking, or discontinuing CYP450 inhibitors. These patients should be evaluated at frequent intervals and dose adjustments considered until stable drug effects are achieved.

Inducers of CYP3A4:

Although clinical studies have not been conducted, CYP450 inducers, such as rifampin, carbamazepine, and phenytoin, may induce the metabolism of oxycodone and, therefore, may cause increased clearance of the drug, which could lead to a decrease in oxycodone plasma concentrations, lack of efficacy, or, possibly, development of abstinence syndrome in a patient who had developed physical dependence to oxycodone. If co-administration with Oxycodone HCl Controlled-Release Tablets is necessary, caution is advised when initiating therapy with, currently taking, or discontinuing CYP450 inducers. These patients should be evaluated at frequent intervals and dose adjustments considered until stable drug effects are achieved.

Inhibitors of CYP2D6:

Oxycodone is metabolized in part to oxymorphone via cytochrome P450 2D6. While this pathway may be blocked by a variety of drugs (e.g., certain cardiovascular drugs including amiodarone and quinidine as well as polycyclic antidepressants), such blockade has not yet been shown to be of clinical significance with this agent. Clinicians should be aware of this possible interaction, however.

Use with CNS Depressants

Oxycodone HCl Controlled-Release Tablets, like all opioid analgesics, should be started at 1/3 to 1/2 of the usual dosage in patients who are concurrently receiving other central nervous system depressants including sedatives or hypnotics, general anesthetics, phenothiazines, centrally acting anti-emetics, tranquilizers, and alcohol because respiratory depression, hypotension, and profound sedation or coma may result. No specific interaction between oxycodone and monoamine oxidase inhibitors has been observed, but caution in the use of any opioid in patients taking this class of drugs is appropriate.

Carcinogenesis and Mutagenesis and Impairment of Fertility

Studies of oxycodone to evaluate its carcinogenic potential have not been conducted.

Oxycodone was not mutagenic in the following assays: Ames Salmonella and E. coli test with and without metabolic activation at doses of up to 5000 µg, chromosomal aberration test in human lymphocytes in the absence of metabolic activation at doses of up to 1500 µg/mL and with activation 48 hours after exposure at doses of up to 5000 µg/mL, and in the in vivo bone marrow micronucleus test in mice (at plasma levels of up to 48 µg/mL). Oxycodone was clastogenic in the human lymphocyte chromosomal assay in the presence of metabolic activation in the human chromosomal aberration test (at greater than or equal to 1250 µg/mL) at 24 but not 48 hours of exposure and in the mouse lymphoma assay at doses of 50 µg/mL or greater with metabolic activation and at 400 µg/mL or greater without metabolic activation.

Pregnancy

Teratogenic Effects - Category B: Reproduction studies have been performed in rats and rabbits by oral administration at doses up to 8 mg/kg and 125 mg/kg, respectively. These doses are 3 and 46 times a human dose of 160 mg/day, based on mg/kg basis. The results did not reveal evidence of harm to the fetus due to oxycodone. There are, however, no adequate and well-controlled studies in pregnant women. Because animal reproduction studies are not always predictive of human response, this drug should be used during pregnancy only if clearly needed.

Labor and Delivery

Oxycodone HCl Controlled-Release Tablets are not recommended for use in women during and immediately prior to labor and delivery because oral opioids may cause respiratory depression in the newborn. Neonates whose mothers have been taking oxycodone chronically may exhibit respiratory depression and/or withdrawal symptoms, either at birth and/or in the nursery.

Nursing Mothers

Low concentrations of oxycodone have been detected in breast milk. Withdrawal symptoms can occur in breast-feeding infants when maternal administration of an opioid analgesic is stopped. Ordinarily, nursing should not be undertaken while a patient is receiving Oxycodone HCl Controlled-Release Tablets because of the possibility of sedation and/or respiratory depression in the infant.

Pediatric Use

Safety and effectiveness of Oxycodone HCl Controlled-Release Tablets have not been established in pediatric patients below the age of 18. It must be remembered that Oxycodone HCl Controlled-Release Tablets cannot be crushed or divided for administration.

Geriatric Use

In controlled pharmacokinetic studies in elderly subjects (greater than 65 years) the clearance of oxycodone appeared to be slightly reduced. Compared to young adults, the plasma concentrations of oxycodone were increased approximately 15%

(see PHARMACOKINETICS AND METABOLISM). Of the total number of subjects (445) in clinical studies of Oxycodone HCl Controlled-Release Tablets, 148 (33.3%) were age 65 and older (including those age 75 and older) while 40 (9.0%) were age 75 and older. In clinical trials with appropriate initiation of therapy and dose titration, no untoward or unexpected side effects were seen in the elderly patients who received Oxycodone HCl Controlled-Release Tablets. Thus, the usual doses and dosing intervals are appropriate for these patients. As with all opioids, the starting dose should be reduced to 1/3 to 1/2 of the usual dosage in debilitated, non-tolerant patients. Respiratory depression is the chief hazard in elderly or debilitated patients, usually following large initial doses in non-tolerant patients, or when opioids are given in conjunction with other agents that depress respiration.

Laboratory Monitoring

Due to the broad range of plasma concentrations seen in clinical populations, the varying degrees of pain, and the development of tolerance, plasma oxycodone measurements are usually not helpful in clinical management. Plasma concentrations of the active drug substance may be of value in selected, unusual or complex cases.

Hepatic Impairment

A study of Oxycodone HCl Controlled-Release Tablets in patients with hepatic impairment indicates greater plasma concentrations than those with normal function. The initiation of therapy at 1/3 to 1/2 the usual doses and careful dose titration is warranted.

Renal Impairment

In patients with renal impairment, as evidenced by decreased creatinine clearance (<60 mL/min), the concentrations of oxycodone in the plasma are approximately 50% higher than in subjects with normal renal function. Dose initiation should follow a conservative approach. Dosages should be adjusted according to the clinical situation.

Gender Differences

In pharmacokinetic studies, opioid-naive females demonstrate up to 25% higher average plasma concentrations and greater frequency of typical opioid adverse events than males, even after adjustment for body weight. The clinical relevance of a difference of this magnitude is low for a drug intended for chronic usage at individualized dosages, and there was no male/female difference detected for efficacy or adverse events in clinical trials.

ADVERSE REACTIONS

The safety of Oxycodone HCl Controlled-Release Tablets was evaluated in double-blind clinical trials involving 713 patients with moderate to severe pain of various etiologies. In open-label studies of cancer pain, 187 patients received Oxycodone HCl Controlled-Release Tablets in total daily doses ranging from 20 mg to 640 mg per day. The average total daily dose was approximately 105 mg per day.

Serious adverse reactions which may be associated with Oxycodone HCl Controlled-Release Tablet therapy in clinical use are those observed with other opioid analgesics, including respiratory depression, apnea, respiratory arrest, and (to an even lesser degree) circulatory depression, hypotension, or shock (see OVERDOSAGE).

The non-serious adverse events seen on initiation of therapy with Oxycodone HCl Controlled-Release Tablets are typical opioid side effects. These events are dose-dependent, and their frequency depends upon the dose, the clinical setting, the patient’s level of opioid tolerance, and host factors specific to the individual. They should be expected and managed as a part of opioid analgesia. The most frequent (>5%) include: constipation, nausea, somnolence, dizziness, vomiting, pruritus, headache, dry mouth, sweating, and asthenia.

In many cases the frequency of these events during initiation of therapy may be minimized by careful individualization of starting dosage, slow titration, and the avoidance of large swings in the plasma concentrations of the opioid. Many of these adverse events will cease or decrease in intensity as Oxycodone HCl Controlled-Release Tablet therapy is continued and some degree of tolerance is developed.

Clinical trials comparing Oxycodone HCl Controlled-Release Tablets with immediate-release oxycodone and placebo revealed a similar adverse event profile between Oxycodone HCl Controlled-Release Tablets and immediate-release oxycodone. The most common adverse events (>5%) reported by patients at least once during therapy were:

TABLE 3
 | Oxycodone HCl Controlled- Release Tablets (n=227) (%) | Immediate-Release (n=225) (%) | Placebo (n=45) (%)
Constipation | (23) | (26) | (7)
Nausea | (23) | (27) | (11)
Somnolence | (23) | (24) | (4)
Dizziness | (13) | (16) | (9)
Pruritus | (13) | (12) | (2)
Vomiting | (12) | (14) | (7)
Headache | (7) | (8) | (7)
Dry Mouth | (6) | (7) | (2)
Asthenia | (6) | (7) | -
Sweating | (5) | (6) | (2)

The following adverse experiences were reported in Oxycodone HCl Controlled-Release Tablets-treated patients with an incidence between 1% and 5%. In descending order of frequency they were anorexia, nervousness, insomnia, fever, confusion, diarrhea, abdominal pain, dyspepsia, rash, anxiety, euphoria, dyspnea, postural hypotension, chills, twitching, gastritis, abnormal dreams, thought abnormalities, and hiccups.

The following adverse reactions occurred in less than 1% of patients involved in clinical trials or were reported in postmarketing experience.

Blood and lymphatic system disorders: lymphadenopathy

Cardiac disorders: palpitations (in the context of withdrawal)

Ear and labyrinth disorders: tinnitus

Endocrine disorders: syndrome of inappropriate antidiuretic hormone secretion (SIADH)

Eye disorders: abnormal vision

Gastrointestinal disorders: dysphagia, eructation, flatulence, gastrointestinal disorder, ileus, increased appetite, stomatitis

General disorders and administration site conditions: chest pain, edema, facial edema, malaise, pain, peripheral edema, thirst, withdrawal syndrome (with and without seizures)

Immune system disorders: anaphylactic or anaphylactoid reaction (symptoms of)

Infections and infestations: pharyngitis

Injury, poisoning and procedural complications: accidental injury

Investigations: hyponatremia, increased hepatic enzymes, ST depression

Metabolism and nutrition disorders: dehydration

Musculoskeletal and connective tissue disorders: neck pain

Nervous system disorders: abnormal gait, amnesia, hyperkinesia, hypertonia (muscular), hypesthesia, hypotonia, migraine, paresthesia, seizures, speech disorder, stupor, syncope, taste perversion, tremor, vertigo

Psychiatric disorders: agitation, depersonalization, depression, emotional lability, hallucination

Renal and urinary disorders: dysuria, hematuria, polyuria, urinary retention, urination impaired

Reproductive system and breast disorders: amenorrhea, decreased libido, impotence

Respiratory, thoracic and mediastinal disorders: cough increased, voice alteration

Skin and subcutaneous tissue disorders: dry skin, exfoliative dermatitis, urticaria

Vascular disorders: vasodilation

OVERDOSAGE

Acute overdosage with oxycodone can be manifested by respiratory depression, somnolence progressing to stupor or coma, skeletal muscle flaccidity, cold and clammy skin, constricted pupils, bradycardia, hypotension, and death.

Deaths due to overdose have been reported with abuse and misuse of Oxycodone HCl Controlled-Release Tablets, by ingesting, inhaling, or injecting the crushed tablets. Review of case reports has indicated that the risk of fatal overdose is further increased when Oxycodone HCl Controlled-Release Tablets are abused concurrently with alcohol or other CNS depressants, including other opioids.

In the treatment of oxycodone overdosage, primary attention should be given to the re-establishment of a patent airway and institution of assisted or controlled ventilation. Supportive measures (including oxygen and vasopressors) should be employed in the management of circulatory shock and pulmonary edema accompanying overdose as indicated. Cardiac arrest or arrhythmias may require cardiac massage or defibrillation.

The pure opioid antagonists such as naloxone or nalmefene are specific antidotes against respiratory depression from opioid overdose. Opioid antagonists should not be administered in the absence of clinically significant respiratory or circulatory depression secondary to oxycodone overdose. In patients who are physically dependent on any opioid agonist including Oxycodone HCl Controlled-Release Tablets, an abrupt or complete reversal of opioid effects may precipitate an acute abstinence syndrome. The severity of the withdrawal syndrome produced will depend on the degree of physical dependence and the dose of the antagonist administered. Please see the prescribing information for the specific opioid antagonist for details of their proper use.

DOSAGE AND ADMINISTRATION

General Principles

OXYCODONE HCl CONTROLLED-RELEASE TABLETS ARE AN OPIOID AGONIST AND A SCHEDULE II CONTROLLED SUBSTANCE WITH AN ABUSE LIABILITY SIMILAR TO MORPHINE. OXYCODONE, LIKE MORPHINE AND OTHER OPIOIDS USED IN ANALGESIA, CAN BE ABUSED AND IS SUBJECT TO CRIMINAL DIVERSION.

OXYCODONE HCl CONTROLLED-RELEASE TABLETS ARE TO BE SWALLOWED WHOLE AND ARE NOT TO BE BROKEN, CHEWED, OR CRUSHED. TAKING BROKEN, CHEWED, OR CRUSHED OXYCODONE HCl CONTROLLED-RELEASE TABLETS LEADS TO RAPID RELEASE AND ABSORPTION OF A POTENTIALLY FATAL DOSE OF OXYCODONE.

One Oxycodone HCl controlled-release 160 mg tablet is comparable to two 80 mg tablets when taken on an empty stomach. With a high-fat meal, however, there is a 25% greater peak plasma concentration following one 160 mg tablet. Dietary caution should be taken when patients are initially titrated to 160 mg tablets (see DOSAGE AND ADMINISTRATION).

Patients should be started on the lowest appropriate dose (see DOSAGE AND ADMINISTRATION; Initiation of Therapy).

In treating pain it is vital to assess the patient regularly and systematically. Therapy should also be regularly reviewed and adjusted based upon the patient's own reports of pain and side effects and the health professional's clinical judgment.

Oxycodone HCl Controlled-Release Tablets are a controlled-release oral formulation of oxycodone hydrochloride indicated for the management of moderate to severe pain when a continuous, around-the-clock analgesic is needed for an extended period of time. The controlled-release nature of the formulation allows Oxycodone HCl Controlled-Release Tablets to be effectively administered every 12 hours (see CLINICAL PHARMACOLOGY; PHARMACOKINETICS AND METABOLISM). While symmetric (same dose AM and PM), around-the-clock, q12h dosing is appropriate for the majority of patients, some patients may benefit from asymmetric (different dose given in AM than in PM) dosing, tailored to their pain pattern. It is usually appropriate to treat a patient with only one opioid for around-the-clock therapy.

Physicians should individualize treatment using a progressive plan of pain management such as outlined by the World Health Organization, the American Pain Society and the Federation of State Medical Boards Model Guidelines. Healthcare professionals should follow appropriate pain management principles of careful assessment and ongoing monitoring (see BOXED WARNING).

Initiation of Therapy

It is critical to initiate the dosing regimen for each patient individually, taking into account the patient's prior opioid and non-opioid analgesic treatment. Attention should be given to:

1. the general condition and medical status of the patient;
2. the daily dose, potency, and kind of the analgesic(s) the patient has been taking;
3. the reliability of the conversion estimate used to calculate the dose of oxycodone;
4. the patient's opioid exposure and opioid tolerance (if any);
5. the Special Instructions for Oxycodone HCl Controlled-Release 80 mg, and 160 mg Tablets, or a Single Dose Greater Than 40 mg; and
6. the balance between pain control and adverse experiences.

Care should be taken to use low initial doses of Oxycodone HCl Controlled-Release Tablets in patients who are not already opioid-tolerant, especially those who are receiving concurrent treatment with muscle relaxants, sedatives, or other CNS active medications (see PRECAUTIONS: Drug-Drug Interactions).

For initiation of Oxycodone HCl Controlled-Release Tablets therapy for patients previously taking opioids, the conversion ratios from Foley, KM. [NEJM, 1985; 313:84-95], found below, are a reasonable starting point, although not verified in well-controlled, multiple-dose trials.

Experience indicates a reasonable starting dose of Oxycodone HCl Controlled-Release Tablets for patients who are taking non-opioid analgesics and require continuous around-the-clock therapy for an extended period of time is 10 mg q12h. If a non-opioid analgesic is being provided, it may be continued. Oxycodone HCl Controlled-Release Tablets should be individually titrated to a dose that provides adequate analgesia and minimizes side effects.

1. Using standard conversion ratio estimates (see Table 4 below), multiply the mg/day of the previous opioids by the appropriate multiplication factors to obtain the equivalent total daily dose of oral oxycodone.
2. When converting from oxycodone, divide the 24-hour oxycodone dose in half to obtain the twice a day (q12h) dose of Oxycodone HCl Controlled-Release Tablets.
3. Round down to a dose which is appropriate for the tablet strengths available (10 mg,20 mg, 40 mg, and 80 mg tablets).
4. Discontinue all other around-the-clock opioid drugs when Oxycodone HCl Controlled-Release Tablet therapy is initiated.
5. No fixed conversion ratio is likely to be satisfactory in all patients, especially patients receiving large opioid doses. The recommended doses shown in Table 4 are only a starting point, and close observation and frequent titration are indicated until patients are stable on the new therapy.
  TABLE 4.
  Multiplication Factors for Converting the Daily Dose of Prior Opiods to the Daily Dose of Oral Oxycodone*
   | (Mg/Day Prior Opiod x Factor = Mg/Day Oral Oxycodone)
   | Oral Prior Opiod | Parenteral Prior Opiod
  Oxycodone | 1 | --
  Codeine | 0.15 | --
  Hydrocodone | 0.9 | --
  Hydromorphone | 4 | 20
  Levorphanol | 7.5 | 15
  Meperidine | 0.1 | 0.4
  Methadone | 1.5 | 3
  Morphine | 0.5 | 3
  * To be used only for conversion to oral oxycodone. For patients receiveing high-dose parenteral opiods, a more conservative conversion is warranted. For example, for high-dose parenteral morphone, use 1.5 instead of 3 as a multiplication factor.

In all cases, supplemental analgesia should be made available in the form of a suitable short-acting analgesic.

Oxycodone HCl Controlled-Release Tablets can be safely used concomitantly with usual doses of non-opioid analgesics and analgesic adjuvants, provided care is taken to select a proper initial dose (see PRECAUTIONS).

Conversion from Transdermal Fentanyl to Oxycodone HCl Controlled-Release Tablets

Eighteen hours following the removal of the transdermal fentanyl patch, Oxycodone HCl Controlled-Release Tablet treatment can be initiated. Although there has been no systematic assessment of such conversion, a conservative oxycodone dose, approximately 10 mg q12h of Oxycodone HCl Controlled-Release Tablets, should be initially substituted for each 25-µg/hr fentanyl transdermal patch. The patient should be followed closely for early titration, as there is very limited clinical experience with this conversion.

Managing Expected Opioid Adverse Experiences

Most patients receiving opioids, especially those who are opioid-naive, will experience side effects. Frequently the side effects from Oxycodone HCl Controlled-Release Tablets are transient, but may require evaluation and management. Adverse events such as constipation should be anticipated and treated aggressively and prophylactically with a stimulant laxative and/or stool softener. Patients do not usually become tolerant to the constipating effects of opioids.

Other opioid-related side effects such as sedation and nausea are usually self-limited and often do not persist beyond the first few days. If nausea persists and is unacceptable to the patient, treatment with antiemetics or other modalities may relieve these symptoms and should be considered.

Patients receiving Oxycodone HCl Controlled-Release Tablets may pass an intact matrix “ghost” in the stool or via colostomy. These ghosts contain little or no residual oxycodone and are of no clinical consequence.

Individualization of Dosage

Once therapy is initiated, pain relief and other opioid effects should be frequently assessed. Patients should be titrated to adequate effect (generally mild or no pain with the regular use of no more than two doses of supplemental analgesia per 24 hours). Patients who experience breakthrough pain may require dosage adjustment or rescue medication. Because steady-state plasma concentrations are approximated within 24 to 36 hours, dosage adjustment may be carried out every 1 to 2 days. It is most appropriate to increase the q12h dose, not the dosing frequency. There is no clinical information on dosing intervals shorter than q12h. As a guideline, the total daily oxycodone dose usually can be increased by 25% to 50% of the current dose at each increase.

If signs of excessive opioid-related adverse experiences are observed, the next dose may be reduced. If this adjustment leads to inadequate analgesia, a supplemental dose of immediate-release oxycodone may be given. Alternatively, non-opioid analgesic adjuvants may be employed. Dose adjustments should be made to obtain an appropriate balance between pain relief and opioid-related adverse experiences.

If significant adverse events occur before the therapeutic goal of mild or no pain is achieved, the events should be treated aggressively. Once adverse events are under control, upward titration should continue to an acceptable level of pain control.

During periods of changing analgesic requirements, including initial titration, frequent contact is recommended between physician, other members of the healthcare team, the patient and the caregiver/family.

Special Instructions for Oxycodone HCl Controlled-Release 80 mg Tablets, or a single dose greater than 40 mg (for use in opioid-tolerant patients only.)

Oxycodone HCl Controlled-Release 80 mg Tablets, or a single dose greater than 40 mg, are for use in opioid-tolerant patients only. A single daily dose greater than 40 mg, or total daily doses greater than 80 mg, may cause fatal respiratory depression when administered to patients who are not tolerant to the respiratory depressant effects of opioids. Patients should be instructed against use by individuals other than the patient for whom it was prescribed, as such inappropriate use may have severe medical consequences, including death.

One Oxycodone HCl Controlled-Release 160 mg tablet is comparable to two 80 mg tablets when taken on an empty stomach. With a high-fat meal, however, there is a 25% greater peak plasma concentration following one 160 mg tablet. Dietary caution should be taken when patients are initially titrated to 160 mg tablets.

Supplemental Analgesia

Most patients given around-the-clock therapy with controlled-release opioids may need to have immediate-release medication available for exacerbations of pain or to prevent pain that occurs predictably during certain patient activities (incident pain).

Maintenance of Therapy

The intent of the titration period is to establish a patient-specific q12h dose that will maintain adequate analgesia with acceptable side effects for as long as pain relief is necessary. Should pain recur then the dose can be incrementally increased to re-establish pain control. The method of therapy adjustment outlined above should be employed to re-establish pain control.

During chronic therapy, especially for non-cancer pain syndromes, the continued need for around-the-clock opioid therapy should be reassessed periodically (e.g., every 6 to 12 months) as appropriate.

Cessation of Therapy

When the patient no longer requires therapy with Oxycodone HCl Controlled-Release Tablets, doses should be tapered gradually to prevent signs and symptoms of withdrawal in the physically dependent patient.

Conversion from Oxycodone HCl Controlled-Release Tablets to Parenteral Opioids

To avoid overdose, conservative dose conversion ratios should be followed.

SAFETY AND HANDLING

Oxycodone HCl Controlled-Release Tablets are solid dosage forms that contain oxycodone, which is a controlled substance. Like morphine, oxycodone is controlled under Schedule II of the Controlled Substances Act.

Oxycodone HCl Controlled-Release Tablets have been targeted for theft and diversion by criminals. Healthcare professionals should contact their State Professional Licensing Board or State Controlled Substances Authority for information on how to prevent and detect abuse or diversion of this product.

HOW SUPPLIED

Oxycodone HCl Controlled-Release Tablets 10 mg are round, unscored, white-colored, convex tablets imprinted with OC on one side and 10 on the other. They are supplied as follows:

NDC 63304-400-01: child-resistant closure, opaque plastic bottles of 100

Oxycodone HCl Controlled-Release Tablets 20 mg are round, unscored, pink-colored, convex tablets imprinted with OC on one side and 20 on the other. They are supplied as follows:

NDC 63304-401-01: child-resistant closure, opaque plastic bottles of 100

Store at 25°C (77°F); excursions permitted between 15°-30°C (59°-86°F).

Dispense in tight, light-resistant container.

CAUTION

DEA Order Form Required.

Distributed by:

Ranbaxy Pharmaceuticals Inc

Jacksonville, FL 32257 USA

U.S. Patent Numbers 5,508,042 and 7,129,248

302389-0A

INFORMATION FOR PATIENTS

OXYCODONE HCl CONTROLLED-RELEASE TABLETS CII

Oxycodone HCl Controlled-Release Tablets, 10 mg

Oxycodone HCl Controlled-Release Tablets, 20 mg

Read this information carefully before you take Oxycodone HCl Controlled-Release Tablets. Also read the information you get with your refills. There may be something new. This information does not take the place of talking with your doctor about your medical condition or your treatment. Only you and your doctor can decide if Oxycodone HCl Controlled-Release Tablets are right for you. Share the important information in this leaflet with members of your household.

What Is The Most Important Information I Should Know About Oxycodone HCl Controlled-Release Tablets?

- Use Oxycodone HCl Controlled-Release Tablets the way your doctor tells you to.
- Use Oxycodone HCl Controlled-Release Tablets only for the condition for which it was prescribed.
- Oxycodone HCl Controlled-Release Tablets are not for occasional (“as needed”) use.
- Swallow the tablets whole. Do not break, crush, dissolve, or chew them before swallowing. Oxycodone HCl Controlled-Release Tablets work properly over 12 hours only when swallowed whole. If a tablet is broken, crushed, dissolved, or chewed, the entire 12 hour dose will be absorbed into your body all at once. This can be dangerous, causing an overdose, and possibly death.
- Keep Oxycodone HCl Controlled-Release Tablets out of the reach of children. Accidental overdose by a child is dangerous and may result in death.
- Prevent theft and misuse. Oxycodone HCl Controlled-Release Tablets contain a narcotic painkiller that can be a target for people who abuse prescription medicines. Therefore, keep your tablets in a secure place, to protect them from theft. Never give them to anyone else. Selling or giving away this medicine is dangerous and against the law.

What are Oxycodone HCl Controlled-Release Tablets?

Oxycodone HCl Controlled-Release Tablets are tablets that come in several strengths and contain the medicine oxycodone (ox-e-KOE-done). This medicine is a painkiller like morphine. Oxycodone HCl Controlled-Release Tablets treat moderate to severe pain that is expected to last for an extended period of time. Use Oxycodone HCl Controlled-Release Tablets regularly during treatment. It contains enough medicine to last for up to twelve hours.

Who Should Not Take Oxycodone HCl Controlled-Release Tablets?

Do not take Oxycodone HCl Controlled-Release Tablets if

- your doctor did not prescribe Oxycodone HCl Controlled-Release Tablets for you.
- your pain is mild or will go away in a few days.
- your pain can be controlled by occasional use of other painkillers.
- you have severe asthma or severe lung problems.
- you have had a severe allergic reaction to codeine, hydrocodone, dihydrocodeine, or oxycodone (such as Tylox, Tylenol with Codeine, or Vicodin). A severe allergic reaction includes a severe rash, hives, breathing problems, or dizziness.
- you had surgery less than 12 - 24 hours ago and you were not taking Oxycodone HCl Controlled-Release Tablets just before surgery.

Your doctor should know about all your medical conditions before deciding if Oxycodone HCl Controlled-Release Tablets are right for you and what dose is best. Tell your doctor about all of your medical problems, especially the ones listed below:

- trouble breathing or lung problems
- head injury
- liver or kidney problems
- adrenal gland problems, such as Addison’s disease
- convulsions or seizures
- alcoholism
- hallucinations or other severe mental problems
- past or present substance abuse or drug addiction

If any of these conditions apply to you, and you haven’t told your doctor, then you should tell your doctor before taking Oxycodone HCl Controlled-Release Tablets.

If you are pregnant or plan to become pregnant, talk with your doctor. Oxycodone HCl Controlled-Release Tablets may not be right for you. Tell your doctor if you are breast feeding. Oxycodone HCl Controlled-Release Tablets will pass through the milk and may harm the baby.

Tell your doctor about all the medicines you take, including prescription and non-prescription medicines, vitamins, and herbal supplements. They may cause serious medical problems when taken with Oxycodone HCl Controlled-Release Tablets, especially if they cause drowsiness.

How Should I Take Oxycodone HCl Controlled-Release Tablets?

- Follow your doctor’s directions exactly. Your doctor may change your dose based on your reactions to the medicine. Do not change your dose unless your doctor tells you to change it. Do not take Oxycodone HCl Controlled-Release Tablets more often than prescribed.
- Swallow the tablets whole. Do not break, crush, dissolve, or chew before swallowing. If the tablets are not whole, your body will absorb too much medicine at one time. This can lead to serious problems, including overdose and death.
- If you miss a dose, take it as soon as possible. If it is almost time for your next dose, skip the missed dose and go back to your regular dosing schedule. Do not take 2 doses at once unless your doctor tells you to.
- In case of overdose, call your local emergency number or Poison Control Center right away.
- Review your pain regularly with your doctor to determine if you still need Oxycodone HCl Controlled-Release Tablets.
- You may see tablets in your stools (bowel movements). Do not be concerned. Your body has already absorbed the medicine.

If you continue to have pain or bothersome side effects, call your doctor.

Stopping Oxycodone HCl Controlled-Release Tablets. Consult your doctor for instructions on how to stop this medicine slowly to avoid uncomfortable symptoms. You should not stop taking Oxycodone HCl Controlled-Release Tablets all at once if you have been taking it for more than a few days.

After you stop taking Oxycodone HCl Controlled-Release Tablets, flush the unused tablets down the toilet.

What Should I Avoid While Taking Oxycodone HCl Controlled-Release Tablets?

- Do not drive, operate heavy machinery, or participate in any other possibly dangerous activities until you know how you react to this medicine. Oxycodone HCl Controlled-Release Tablets can make you sleepy.
- Do not drink alcohol while using Oxycodone HCl Controlled-Release Tablets. It may increase the chance of getting dangerous side effects.
- Do not take other medicines without your doctor’s approval. Other medicines include prescription and non-prescription medicines, vitamins, and supplements. Be especially careful about products that make you sleepy.

What are the Possible Side Effects of Oxycodone HCl Controlled-Release Tablets?

Call your doctor or get medical help right away if

- your breathing slows down
- you feel faint, dizzy, confused, or have any other unusual symptoms

Some of the common side effects of Oxycodone HCl Controlled-Release Tablets are nausea, vomiting, dizziness, drowsiness, constipation, itching, dry mouth, sweating, weakness, and headache. Some of these side effects may decrease with continued use.

There is a risk of abuse or addiction with narcotic painkillers. If you have abused drugs in the past, you may have a higher chance of developing abuse or addiction again while using Oxycodone HCl Controlled-Release Tablets.

These are not all the possible side effects of Oxycodone HCl Controlled-Release Tablets. For a complete list, ask your doctor or pharmacist.

General Advice About Oxycodone HCl Controlled-Release Tablets

- Do not use Oxycodone HCl Controlled-Release Tablets for conditions for which it was not prescribed.
- Do not give Oxycodone HCl Controlled-Release Tablets to other people, even if they have the same symptoms you have. Sharing is illegal and may cause severe medical problems, including death.

This leaflet summarizes the most important information about Oxycodone HCl Controlled-Release Tablets. If you would like more information, talk with your doctor. Also, you can ask your pharmacist or doctor for information about Oxycodone HCl Controlled-Release Tablets that is written for health professionals.

Rx Only

Distributed by:

Ranbaxy Pharmaceuticals Inc

Jacksonville, FL 32257 USA

302389-0A Rev 09/2009

PACKAGE LABEL. PRINCIPAL DISPLAY PANEL

Container Label 10 mg
Container Label 20 mg